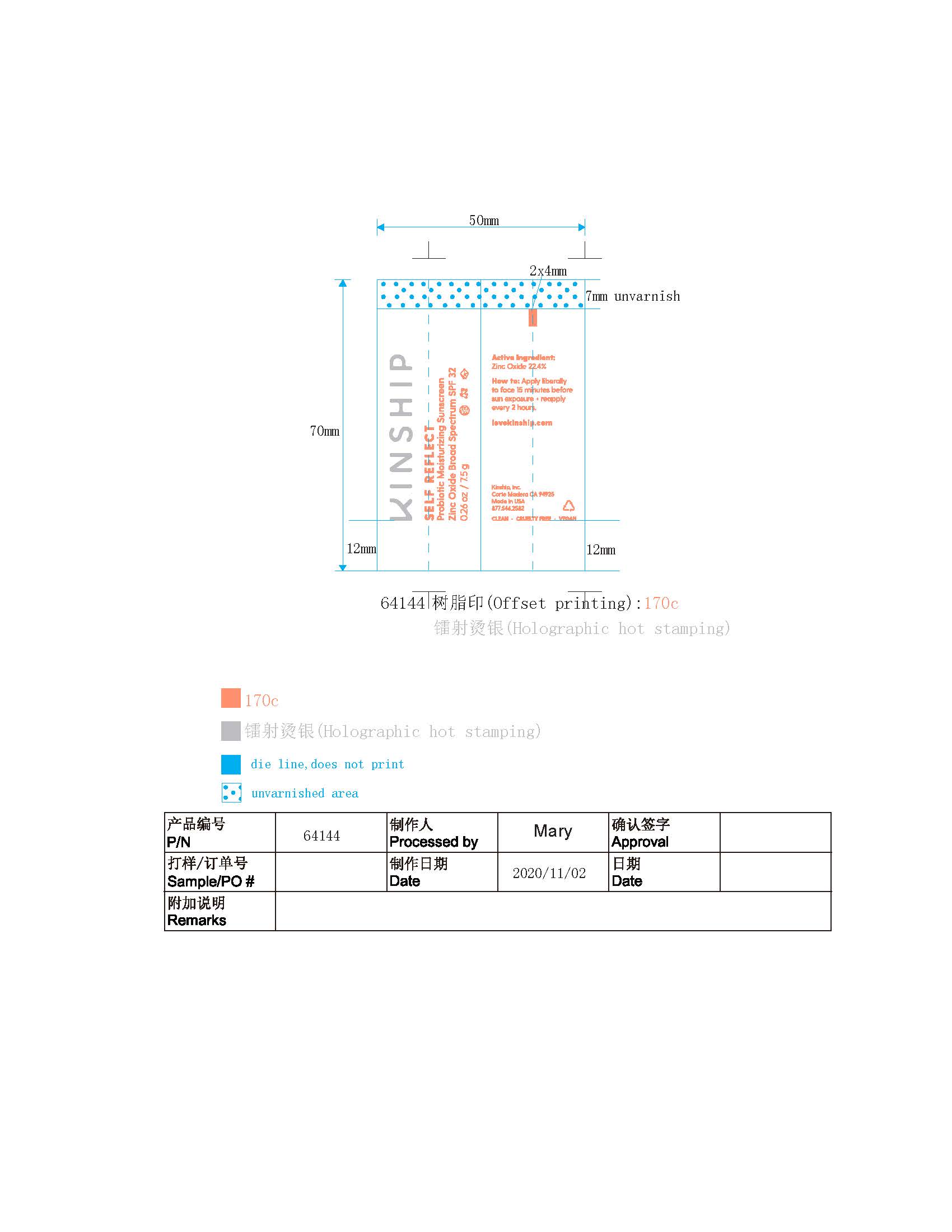 DRUG LABEL: MOISTURIZER
NDC: 61354-048 | Form: CREAM
Manufacturer: OXYGEN DEVELOPMENT, LLC
Category: otc | Type: HUMAN OTC DRUG LABEL
Date: 20220429

ACTIVE INGREDIENTS: ZINC OXIDE 22.4 mg/100 mg
INACTIVE INGREDIENTS: GLYCERIN; WATER; CETOSTEARYL ALCOHOL; COCONUT ALKANES; ALOE VERA LEAF; APPLE; COCO GLUCOSIDE; LACTOBACILLUS REUTERI

Self Reflect Probiotic Moisturizing Sunscreen Zinc Oxide Broad Spectrum SPF 32

Active Ingredients

Zinc Oxide 22.40%

Purpose

Sunscreen

Uses

- Helps prevent sunburn.
- If used as directed with other sun protection measures (see Directions), decreases the risk of skin cancer and early skin aging caused by the sun.

Warnings

For external use only.

Do not use on damaged or broken skin.

When using this product keep out of eyes. Rinse with water to remove.

Stop use and ask a doctor if rash occurs.

Keep out of reach of children. If product is swallowed, get medical help or contact a Poison Control Center right away.

Directions

- Apply liberally 15 minutes before sun exposure.
- Use a water resistant sunscreen if swimming or sweating.
- Reapply at least every 2 hours.
- Sun Protection Measures: Spending time in the sun increases your risk of skin cancer an early skin aging. To decrease this risk, regularly use a sunscreen with a Broad Spectrum SPF value of 15 or higher and other sun protection measures including:
- limit time in the sun, especially from 10am-2pm
- wear long-sleeved shirts, pants hats and sunglasses
- Children under 6 months of age: Ask a doctor.

Other Information

Proect this product from excessive heat and direct sun.

Inactive ingredients

Water(Aqua), Caprylic/Capric Triglyceride, Coconut Alkanes, Cetearyl Alcohol, Glycerin, Aloe Barbadensis Leaf Juice, Pyrus Males (Apple) Fruit Extract, Coco-Glucoside, Lactobacillus Ferment, Rubus Idaeus(red Raspberry) Seed oil, Cocos Nucifera(Coconut) Liquid Endosperm, Curcuma Longa (Turmeric) Rhizomes Oil, Butyrospermum parkii nut Extract, Hydrolyzed Jojoba Esters, Tocopherol, Dipotassium Glycyrrhizate, Vanilla Planifolia Fruit Extract, Glycyrrhiza Glabra(Licorice) Root Extract, Butylene Glycol, Isostearic Acid, Lecithin, Polyglyceryl-3 Polyricinoleate, Polyhydroxystearic Acid, Coco-Caprylate/Caprate, Caprylyl/Capryl Glucoside, Sclerotium Gum, Cetearyl Glucoside, Ethylhexylglycerin, Xantham Gum, Octyldodecanol, Tapioca Startch, Citric Acid, Sorbitan Oleate, Phenoxyethanol, Sodium Benzoate, Potassium Sorbate, May contain +/- Iron Oxides (CI 77491, CI 77492).

Questions or comments?

Call toll free (877) 546-2582